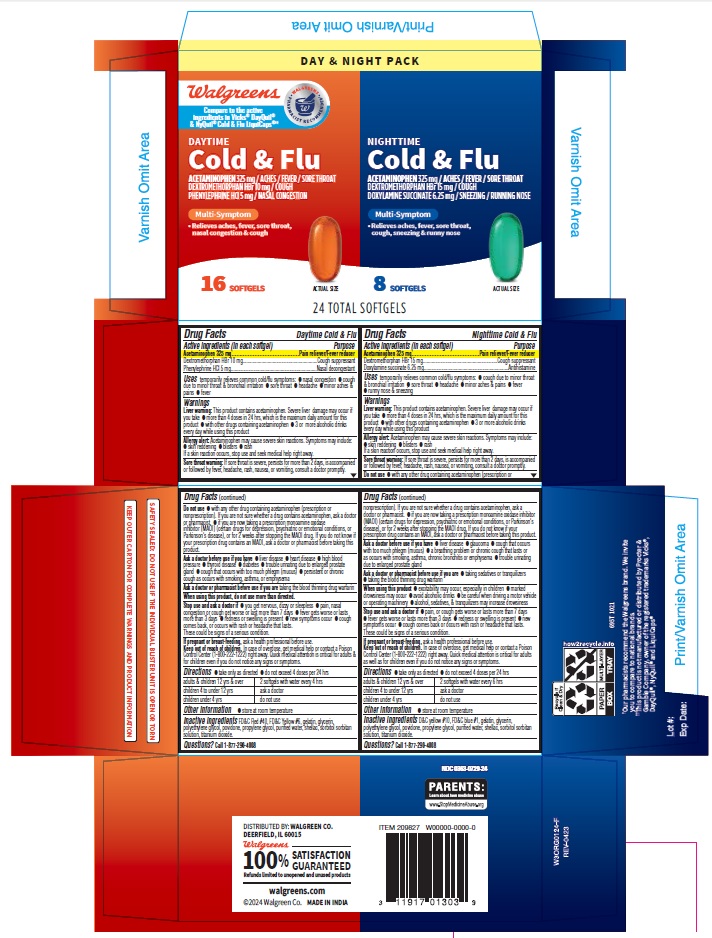 DRUG LABEL: Daytime Nighttime Cold and Flu
NDC: 0363-0729 | Form: KIT | Route: ORAL
Manufacturer: WALGREENS
Category: otc | Type: HUMAN OTC DRUG LABEL
Date: 20240319

ACTIVE INGREDIENTS: ACETAMINOPHEN 325 mg/1 1; DEXTROMETHORPHAN HYDROBROMIDE 10 mg/1 1; PHENYLEPHRINE HYDROCHLORIDE 5 mg/1 1; DEXTROMETHORPHAN HYDROBROMIDE 15 mg/1 1; ACETAMINOPHEN 325 mg/1 1; DOXYLAMINE SUCCINATE 6.25 mg/1 1
INACTIVE INGREDIENTS: FD&C RED NO. 40; POLYETHYLENE GLYCOL, UNSPECIFIED; POVIDONE; SORBITAN; TITANIUM DIOXIDE; FD&C YELLOW NO. 6; SHELLAC; WATER; GELATIN; GLYCERIN; PROPYLENE GLYCOL; FD&C BLUE NO. 1; GELATIN; POVIDONE; WATER; POLYETHYLENE GLYCOL, UNSPECIFIED; SHELLAC; TITANIUM DIOXIDE; PROPYLENE GLYCOL; SORBITAN; D&C YELLOW NO. 10; GLYCERIN

695T 0363 0729 WALGREENS - Daytime Nighttime Cold & Flu

ACTIVE INGREDIENT

Daytime Cold & Flu
Active ingredients (in each softgel)
Acetaminophen 325 mg
Dextromethorphan HBr 10 mg
Phenylephrine HCl 5 mg

Nighttime Cold & Flu
Active ingredients (in each softgel)
Acetaminophen 325 mg
Dextromethorphan HBr 15 mg
Doxylamine succinate 6.25 mg

PURPOSE

Daytime Cold & Flu
Purpose
Pain reliever/fever reducer
Cough suppressant
Nasal decongestant

Nighttime Cold & Flu
Purpose
Pain reliever/fever reducer
Cough suppressant
Antihistamine

Uses
temporarily relieves common cold/flu symptoms:

- nasal congestion (Daytime only)
- cough due to minor throat & bronchial irritation
- sore throat
- headache
- minor aches and pains
- fever
- runny nose and sneezing (Nighttime only)

Warnings
Liver warning: This product contains acetaminophen. Severe liver damage may occur if you take:

- more than 4 doses in 24 hrs, which is the maximum daily amount for this product
- wilh other drugs containing acetaminophen
- 3 or more alcoholic drinks every day while using this product

Sore throat warning: If sore throat is severe, persists for more than 2 days, is accompanied or
followed by fever, headache, rash, nausea, or vomiting, consult a doctor promptly.

Do not use

- with any other drug containing acetaminophen (prescription or nonprescription). If you are not sure whether a drug contains acetaminophen, ask a doctor or pharmacist.
- if you are now taking a prescription monoamine oxidase inhibitor (MAOI) (certain drugs for depression, psychiatric, or emotional conditions, or Parkinson's disease), or for 2 weeks after stopping the MAOI drug. If you do not know if your prescription drug contains an MAOI, ask a doctor or pharmacist before taking this product.

Ask a doctor before use if you have

- liver disease
- heart disease (Daytime only)
- high blood pressure (Daytime only)
- thyroid disease (Daytime only)
- diabetes (Daytime only)
- trouble urinating due to enlarged prostate gland
- cough that occurs with too much phlegm (mucus)
- persistent or chronic cough as occurs with smoking, asthma, or emphysema (Daytime only)
- glaucoma (Nighttime only)
- a breathing problem or chronic cough that lasts or as occurs with smoking, asthma,chronic bronchitis or emphysema (Nighttime only)

Ask a doctor or pharmacist before use if you are

- taking the blood thinning drug warfarin
- taking sedatives or tranquilizers (Nighttime only)

When using this product

- do not use more than directed (Daytime only)
- excitability may occur, especially in children (Nighttime only)
- marked drowsiness may occur (Nighttime only)
- avoid alcoholic drinks (Nighttime only)
- be careful when driving a motor vehicle or operating machinery (Nighttime only)
- alcohol, sedatives, & tranquilizers may increase drowsiness (Nighttime only)

Stop use and ask a doctor If

- you get nervous, dizzy or sleepless (Daytime only)
- pain, nasal congestion or cough get worse or last more than 7days (Daytime only)
- fever gets worse or lasts more than 3 days
- redness or swelling is present
- new symptoms occur
- cough comes back or occurs with rash or headache that lasts.
- pain, or cough gets worse or lasts more than 7days (Nighttime only)
- These could be signs of a serious condition.

PREGNANCY OR BREAST FEEDING

If pregnant or breast-feeding, ask a health professional before use.

Keep out of reach of children.
In case of overdose, get medical help or contact a Poison Control Center righl away (1-800-222-1222). Quick medical attention is critical for adults & for children even if you do not notice any signs or symptoms.

Directions

- take only as directed
- do not exceed 4 doses per 24 hrs

adults & children 12yrs & over: 2 softgels with water every 6 hrs(Nighttime only)
2 softgels with water every 4 hrs (Daytime only)
children 4 to under 12 yrs: ask a doctor
children under 4 yrs: do not use

OTHER INFORMATION

- store at room temperature

Inactive ingredients (Daytime only)
FD&C red # 40, FD&C yellow #6, gelatin, glycerin, polyethylene glycol, povidone, propylene glycol, purified water, shellac, sorbitol sorbitan solution, titanium dioxide.
Inactive ingredients (Nighttime only)
FD&C blue #1, FD&C yellow #10, gelatin, glycerin, polyethylene glycol, povidone, propylene glycol, purified water, shellac, sorbitol sorbitan solution, titanium dioxide.

Questions? Call 1-877-290-4008